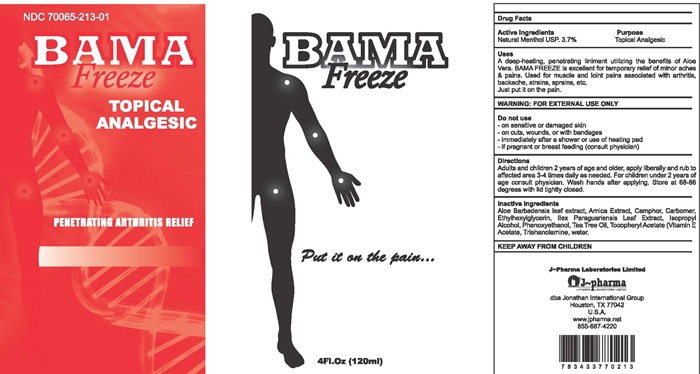 DRUG LABEL: BAMA Freeze
NDC: 70065-213 | Form: LINIMENT
Manufacturer: Jonathan International, Inc.
Category: otc | Type: HUMAN OTC DRUG LABEL
Date: 20150902

ACTIVE INGREDIENTS: MENTHOL 3.7 g/100 mL
INACTIVE INGREDIENTS: CAMPHOR (NATURAL); ALOE VERA LEAF; ARNICA MONTANA; CARBOMER 940; ETHYLHEXYLGLYCERIN; ILEX PARAGUARIENSIS LEAF; ISOPROPYL ALCOHOL; PHENOXYETHANOL; TEA TREE OIL; .ALPHA.-TOCOPHEROL ACETATE; TROLAMINE; WATER

Drug Facts

Active Ingredients

Natural Menthol USP, 3.7%

Purpose

Topical Analgesic

Keep out of reach of children

KEEP AWAY FROM CHILDREN

Uses

A deep-healing, penetrating liniment utilizing the benefits of Aloe Vera, BAMA FREEZE is excellent for temporary relief of minor aches & pains. Used for muscle and joint pains associated with arthritis, bachache, strains, sprains, etc. Just put it on the pain.

WARNING:

FOR EXTERNAL USE ONLY

Do not use

- on sensitive or damaged skin
- on cuts, wounds, or with bandages
- immediately after a shower or use of a heating pad
- if pregnant or breasr feeding (consult a physician)

Directions

Adults and children 2 years of age and older, apply liberally and rub to affected area 3-4 times daily as needed. For children under 2 years of age consult physician. Wash hands after applying. Store at 68086 degrees with lid tightly closed.

Inactive Ingredients

Aloe Barbadenis leaf extractArnica Extract, Camphor, Carbomer, Ethylhexylglycerin, Ilex Paraguariensis Leaf Extract, Isopropyl Alcohol, Phenoxyethanol, Tea Tree Oil, Tocopheryl Acetate (Vitamin E Acetate), Triethanolamine, water

BAMA Freeze product label

NDC 70065-213-01

BAMA Freeze

TOPICAL ANALGESIC

PENETRATING ARTHRITIS RELIEF

Put it on the pain...

4 Fl. Oz (120 ml)

J-Pharma Limited

dba Jonathan International Group

Houston, TX 77042

U.S.A.

www.jpharma.net

855-667-4220